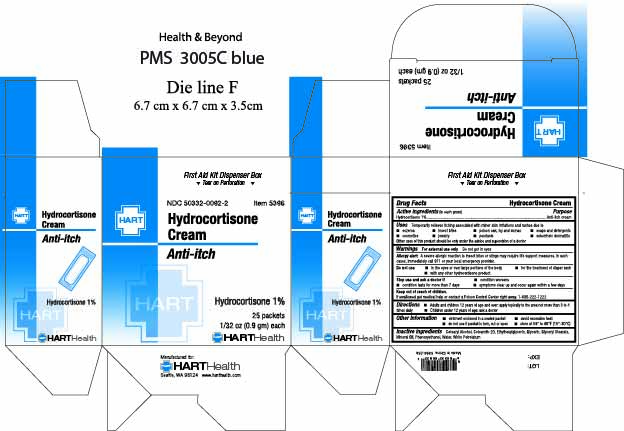 DRUG LABEL: HYDROCORTISONE
NDC: 50332-0092 | Form: CREAM
Manufacturer: HART Health
Category: otc | Type: HUMAN OTC DRUG LABEL
Date: 20251210

ACTIVE INGREDIENTS: HYDROCORTISONE ACETATE 10 mg/1 g
INACTIVE INGREDIENTS: CETEARYL ALCOHOL; CETEARETH-20; ETHYLHEXYLGLYCERIN; GLYCERIN; MINERAL OIL; WHITE PETROLATUM; PHENOXYETHANOL; WATER; GLYCERYL STEARATE

HYDROCORTISONE CREAM

Active Ingredient (in each gram): Hydrocortisone 1%

Purpose: anti-itch cream

Uses

Temporarily relieves itching associated with minor skin irritations and rashes due to

- eczema
- insect bites
- poison oak, ivy and sumac
- soaps and detergents
- cosmetics
- jewelry
- psoriasis
- seborrheic dermatitis

Other uses of this product should be only under the advice and supervision of a doctor

Warnings: For external use only

Do not get in eyes

Allergy alert: A severe allergic reaction to insect bites or stings may require life support measures. In such cases, immediately call 911 or your clocal emergency provider.

Do not use:

- in the eyes or over large portions of the body
- for the treatment of diaper rash
- with any other hydrocortisone product

Stop use and ask a doctor if:

- condition worsens
- condition lasts for more than 7 days
- symptoms clear up and occur again within a few days

Keep out of reach of children. If swallowed get medical help or contact a Poison Control Center right away. 1-800-222-1222

Directions:

- Adults and children 12 years of age and over: apply topically to the area not more than 3 to 4 times daily.
- Children under 12 years of age: ask a doctor

OTHER SAFETY INFORMATION

- ointment enclosed in a sealed packet
- avoid excessive heat
- do not use if packet is torn, cut or open
- store at 59° to 86°F (15°-30°C)

INACTIVE INGREDIENT

Inactive Ingredients: Cetearyl Alcohol, Ceteareth-20, Ethylhexylglycerin, Glycerin, Glyceryl Stearate, Mineral Oil, White Petrolatum, Phenoxyethanol, Water